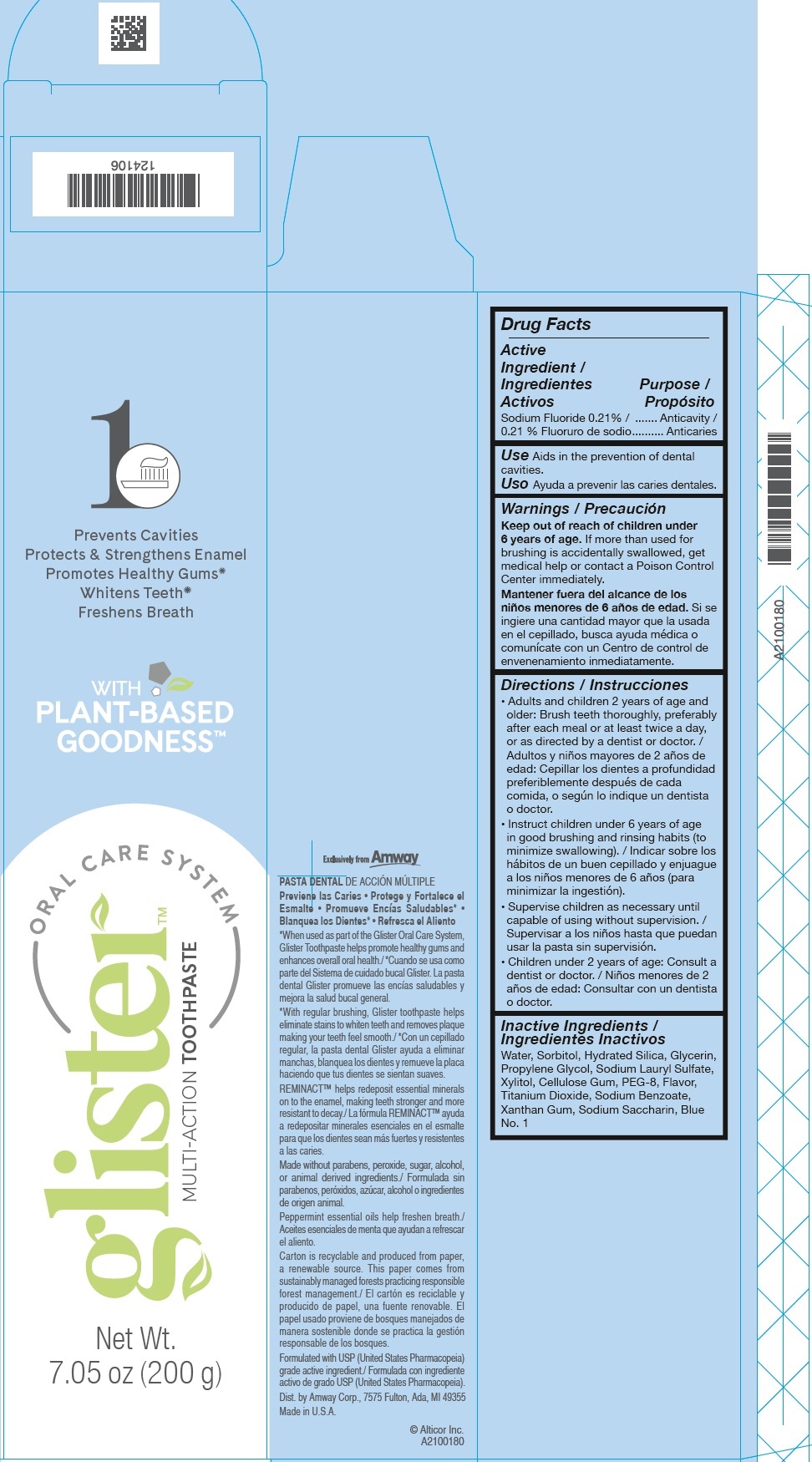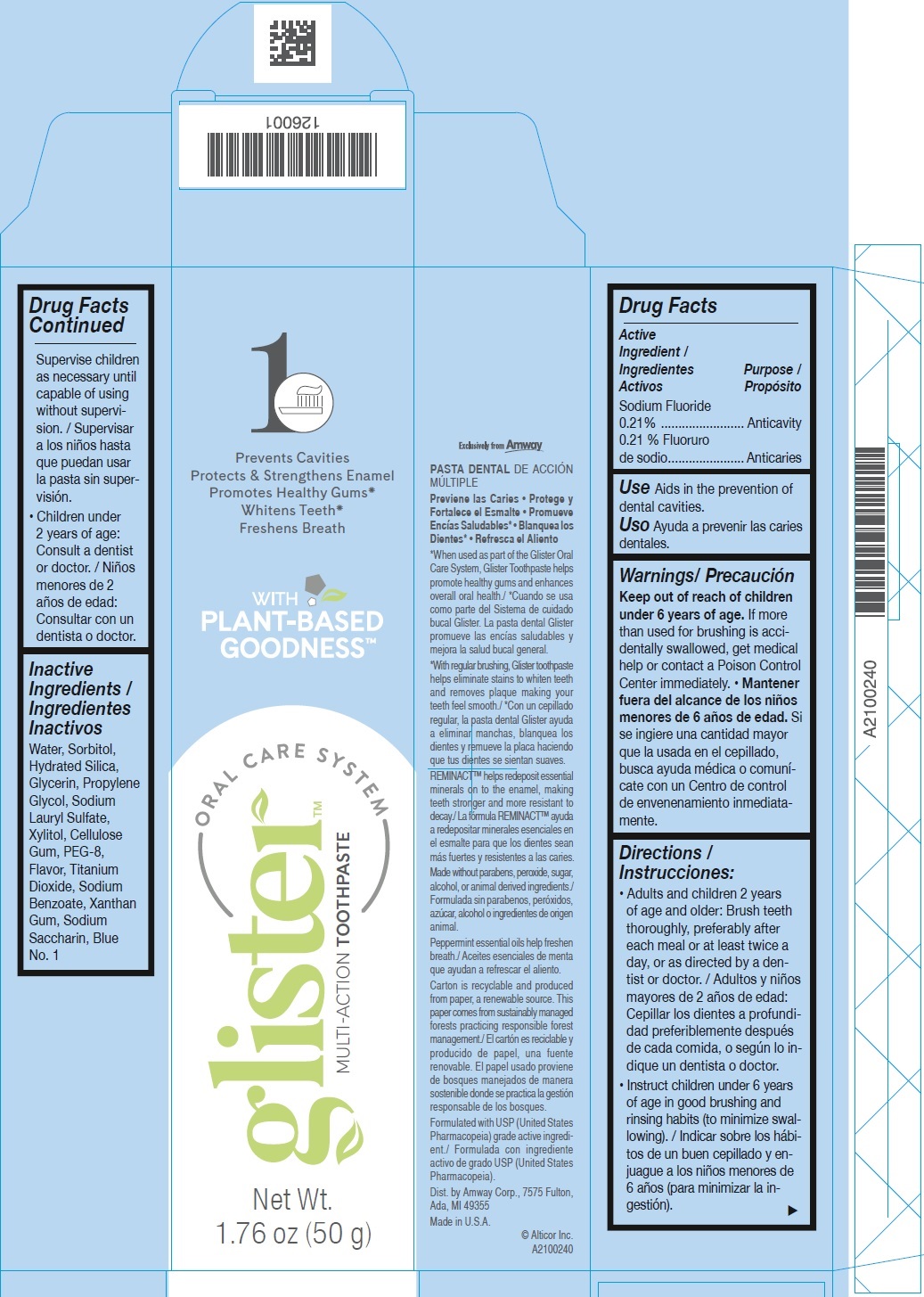 DRUG LABEL: Glister Multi-Action
NDC: 10056-415 | Form: PASTE, DENTIFRICE
Manufacturer: Access Business Group LLC
Category: otc | Type: HUMAN OTC DRUG LABEL
Date: 20231023

ACTIVE INGREDIENTS: SODIUM FLUORIDE 2.1 mg/1 g
INACTIVE INGREDIENTS: WATER; SORBITOL; HYDRATED SILICA; GLYCERIN; PROPYLENE GLYCOL; SODIUM LAURYL SULFATE; XYLITOL; CARBOXYMETHYLCELLULOSE SODIUM, UNSPECIFIED; POLYETHYLENE GLYCOL 400; TITANIUM DIOXIDE; SODIUM BENZOATE; XANTHAN GUM; SACCHARIN SODIUM; FD&C BLUE NO. 1

Glister Multi-Action Toothpaste

Active Ingredient

Sodium Fluoride 0.21%

Purpose

Anticavity

Use

Aids in the prevention of dental cavities.

Warnings

Keep out of reach of children

If more than used for brushing is accidentally swallowed, get medical help or contact a Poison Control Center immediately. under 6 years of age.

Directions

• Adults and children 2 years of age and older: Brush teeth thoroughly, preferably after each meal or at least twice a day, or as directed by a dentist or doctor.

• Instruct children under 6 years of age in good brushing and rinsing habits (to minimize swallowing).

Supervise children as necessary until capable of using without supervision.

• Children under 2 years of age: Consult a dentist or doctor.

Inactive Ingredients

Water, Sorbitol, Hydrated Silica, Glycerin, Propylene Glycol, Sodium Lauryl Sulfate, Xylitol, Cellulose Gum, PEG-8, Flavor, Titanium Dioxide, Sodium Benzoate, Xanthan Gum, Sodium Saccharin, Blue No. 1